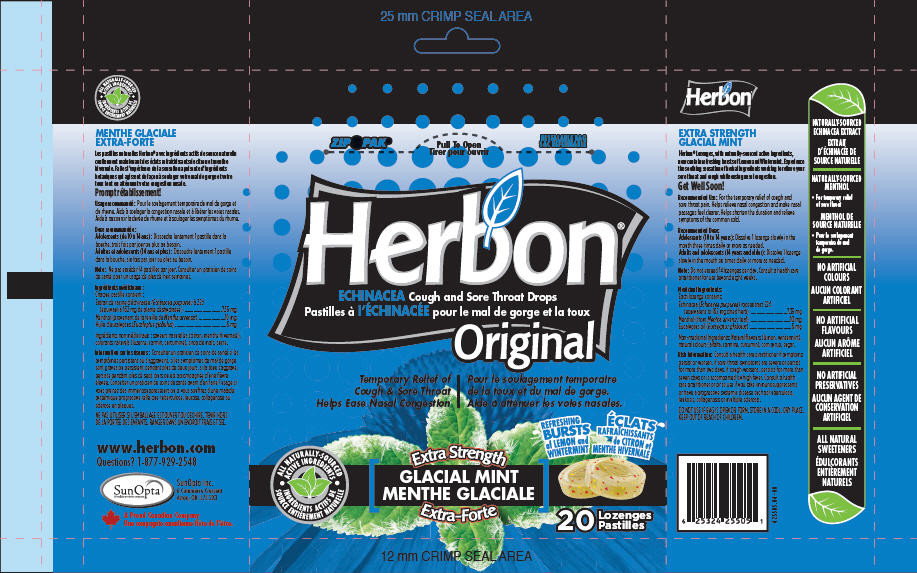 DRUG LABEL: Herbon Glacial Mint
NDC: 44597-5505 | Form: LOZENGE
Manufacturer: Purity Life Division of SunOpta
Category: otc | Type: HUMAN OTC DRUG LABEL
Date: 20090909

ACTIVE INGREDIENTS: Echinacea Purpurea 7.35 mg/1 1; Menthol 10 mg/1 1; Eucalyptus Oil 6 mg/1 1
INACTIVE INGREDIENTS: Sucrose 2150.04 mg/1 1; Corn Syrup

INDICATIONS AND USAGE

Recommended Use: For the temporary relief of cough and sore throat pain. Helps relieve nasal congestion and make nasal passages feel clearer. Helps shorten the duration and relieve symptoms of the common cold.

Recommended Dose:

Adolescents (10 to 14 years): Dissolve 1 lozenge slowly in the mouth three times daily or more as needed.

Adults and adolescents (14 years and older): Dissolve 1 lozenge slowly in the mouth six times daily or more as needed.

Note: Do not exceed 14 lozenges per day. Consult a health care practitioner for use beyond eight weeks.

Medicinal Ingredients:

Each lozenge contains:

Echinacea (Echinacea purpurea) root extract 22:1
(equivalent to 162 mg dried herb) ................................7.35 mg

Menthol (from Mentha arvensis leaf) ...................................10 mg

Eucalyptus oil (Eucalyptus globulus) .....................................6 mg

INACTIVE INGREDIENT

Non-medicinal Ingredients: Natural flavours (lemon, wintermint), natural colours (alfalfa, carmine, curcumin), corn syrup, sugar.

WARNINGS

Risk Information: Consult a health care practitioner if symptoms persist or worsen, if sore throat symptoms are severe or persist for more than two days, if cough worsens, persists for more than seven days or is accompanied by high fever. Consult a health care practitioner prior to use if you take immunosuppressants or have a progressive systemic disease such as tuberculosis, leukosis, collagenosis or multiple sclerosis.

DO NOT USE IF BAG IS OPEN OR TORN.

STORAGE AND HANDLING

STORE IN A COOL, DRY PLACE.

KEEP OUT OF REACH OF CHILDREN.

PRINCIPAL DISPLAY PANEL - 20 Lozenge Bag

Herbon®

ECHINACEA Cough and Sore Throat Drops

Original

Temporary Relief of
Cough & Sore Throat
Helps Ease Nasal Congestion

ALL NATURALLY-SOURCED
ACTIVE INGREDIENTS

Extra Strength

GLACIAL MINT

REFRESHING
BURTS
of LEMON and
WINTERMINT

20 Lozenges